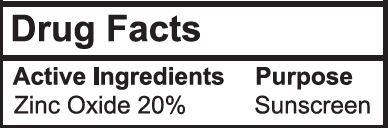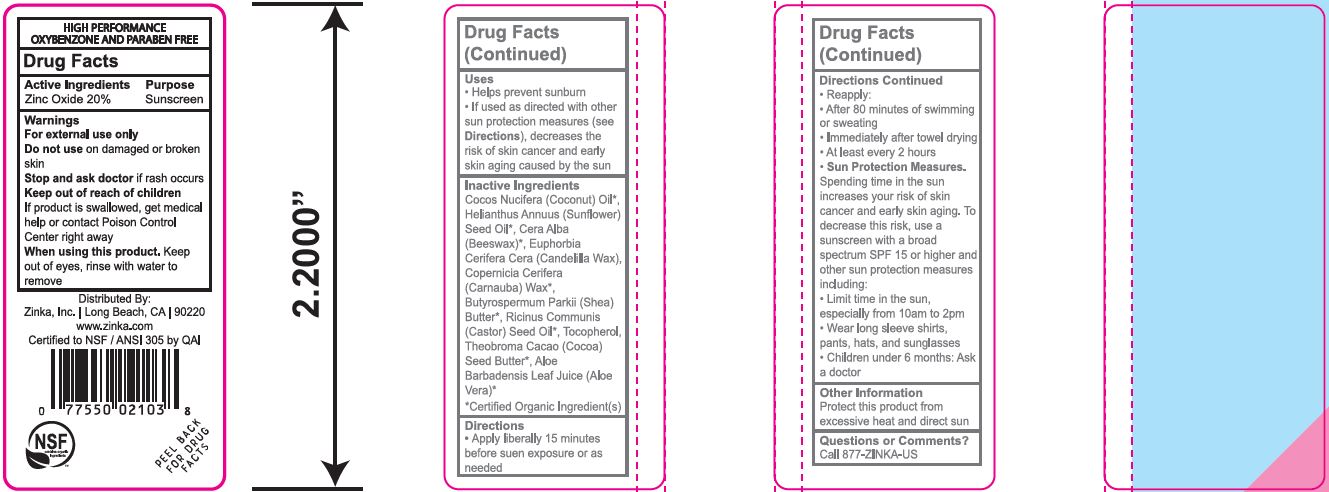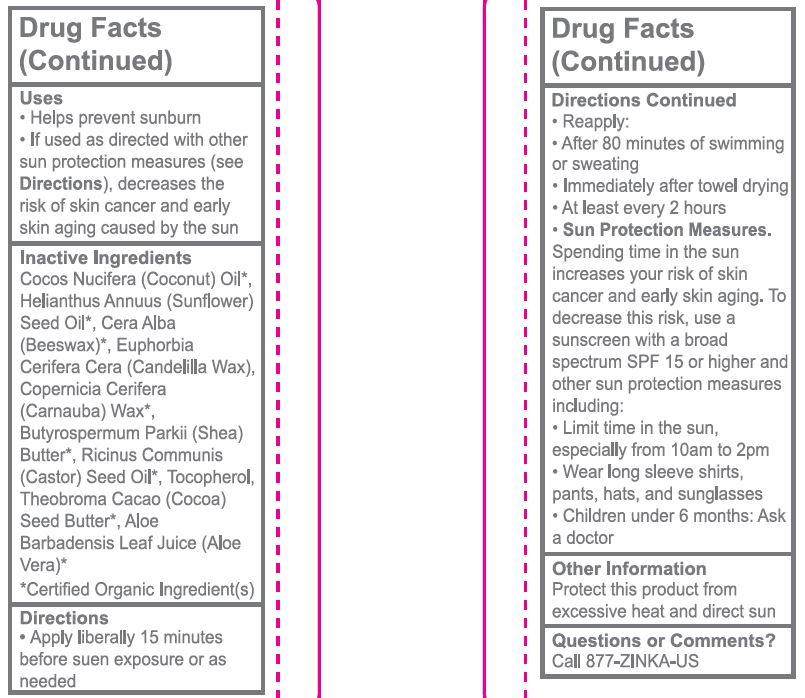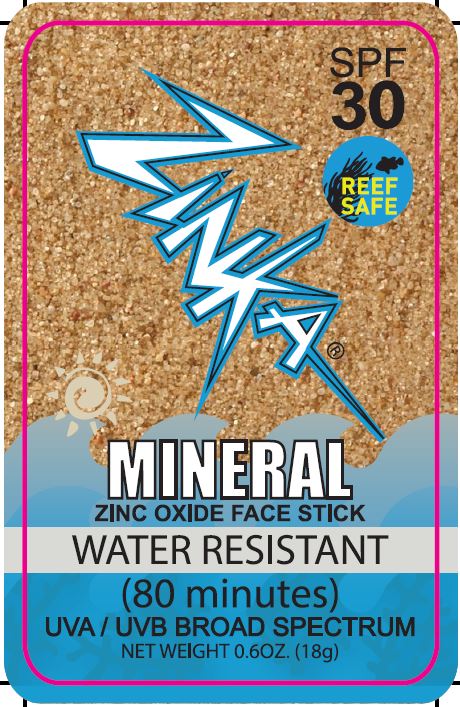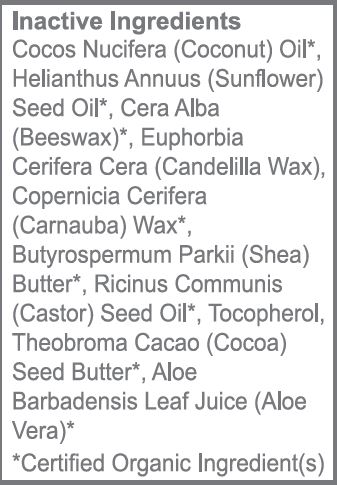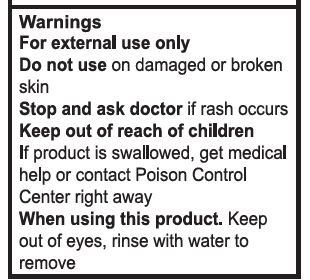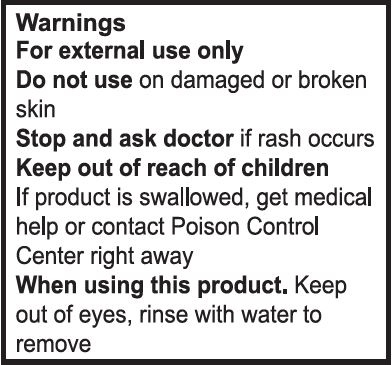 DRUG LABEL: Sunscreen
NDC: 62932-255 | Form: STICK
Manufacturer: Private Label Select Ltd CO
Category: otc | Type: HUMAN OTC DRUG LABEL
Date: 20211230

ACTIVE INGREDIENTS: ZINC OXIDE 20 g/100 g
INACTIVE INGREDIENTS: CANDELILLA WAX; .ALPHA.-TOCOPHEROL, D-; .BETA.-TOCOPHEROL; .GAMMA.-TOCOPHEROL; .DELTA.-TOCOPHEROL; SUNFLOWER OIL; ALOE VERA LEAF; COCONUT OIL; WHITE WAX; CARNAUBA WAX; SHEA BUTTER; CASTOR OIL; COCOA BUTTER

Zinka, Mineral Zinc Oxide Face Stick SPF 30